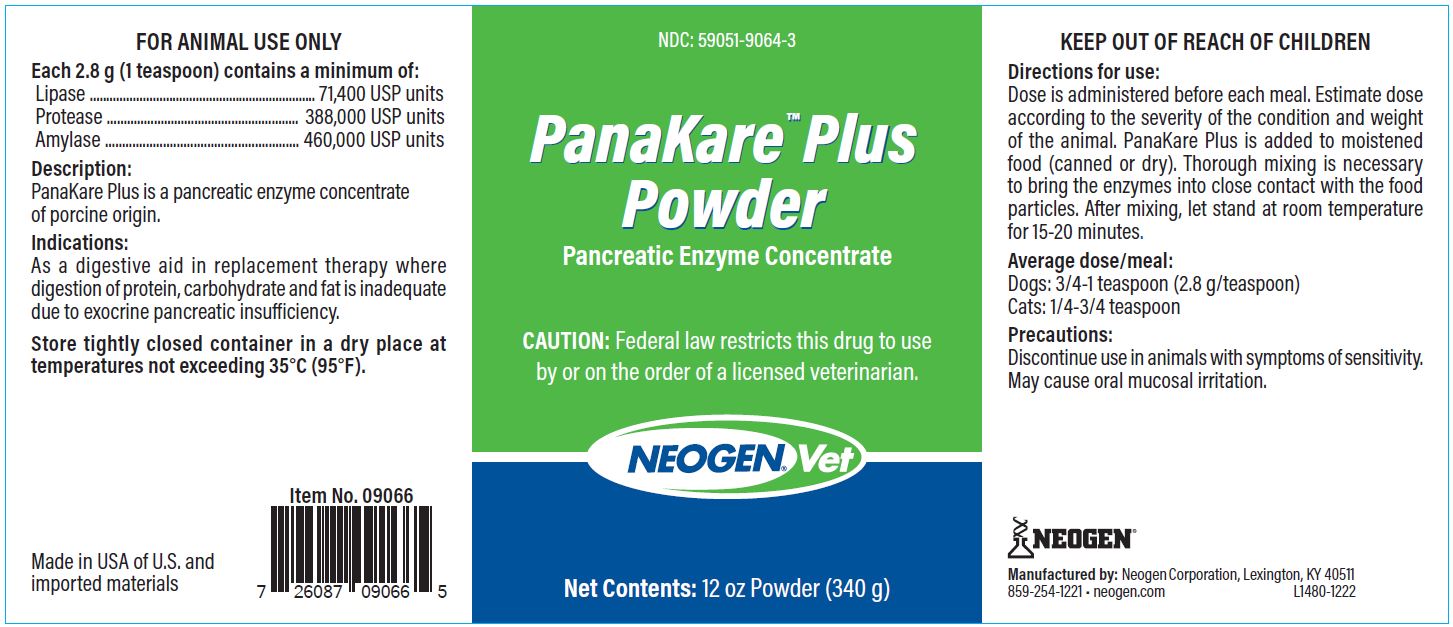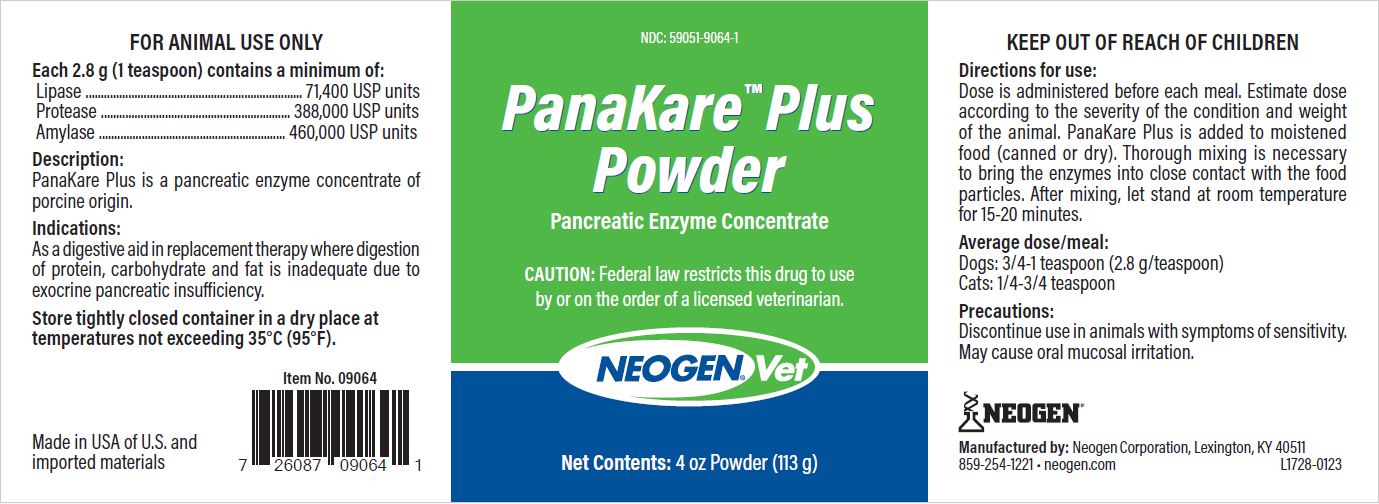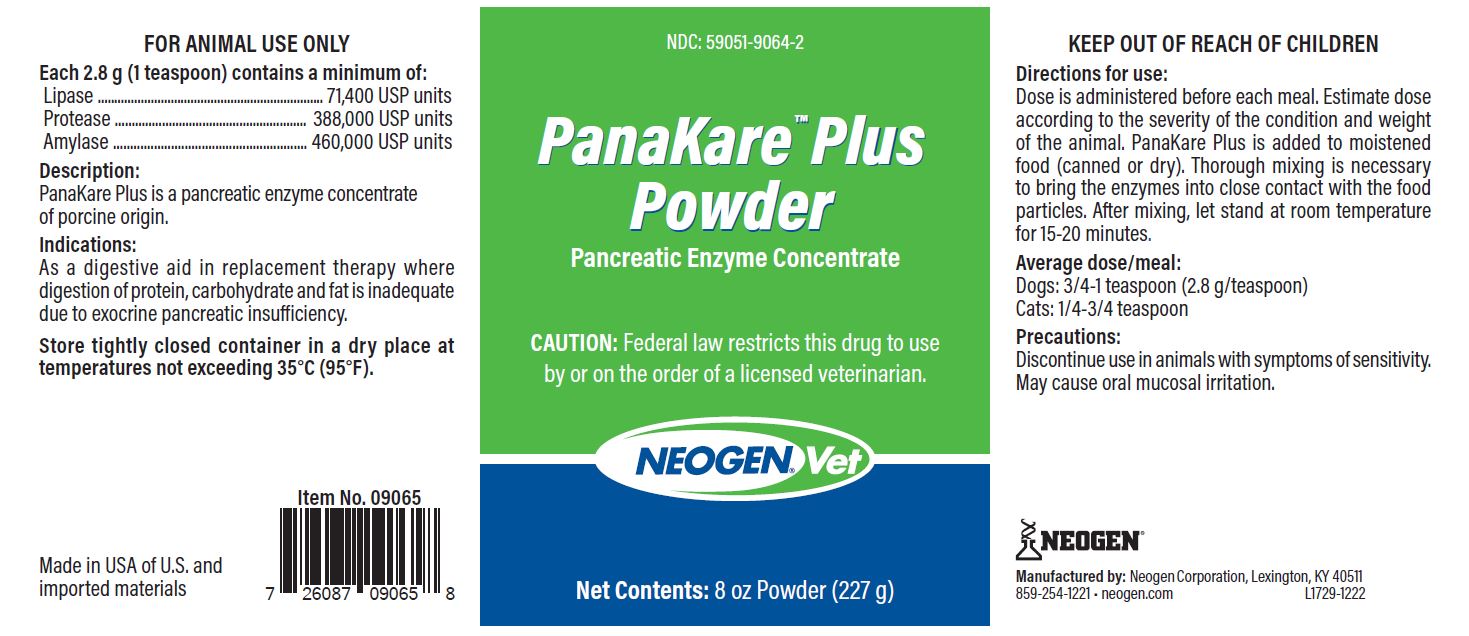 DRUG LABEL: PanaKare Plus
NDC: 59051-9064 | Form: Powder
Manufacturer: Neogen Corporation-Mercer
Category: animal | Type: PRESCRIPTION ANIMAL DRUG LABEL
Date: 20240123

ACTIVE INGREDIENTS: PANCRELIPASE LIPASE 71400 [iU]/2.8 g; PANCRELIPASE AMYLASE 460000 [iU]/2.8 g; PANCRELIPASE PROTEASE 388000 [iU]/2.8 g

PANAKARE PLUS POWDER

FOR ANIMAL USE ONLY

COMPONENTS

Each 2.8 grams (1 teaspoon) contains a minimum of:

Lipase..............................71,400 USP units

Protease.........................388,000 USP units

Amylase..........................460,000 USP units

Description

PanaKare Plus is a pancreatic enzyme concentrate of porcine origin.

Precautions:

Discontinue use in animals with symptoms of sensitivity. May cause oral mucosal irritation.

Made in the USA of U.S and imported materials

Manufactured by: Neogen Corporation

Lexington, KY 40511 859-254-1221

neogen.com

KEEP OUT OF REACH OF CHILDREN

Indications:

As a digestive aid in replacement therapy where digestion of protein, carbohydrate and fat is inadequate due to exocrine pancreatic insufficiency.

Directions for use:

Dose is administered before each meal. Estimate dose according to the severity of the condition and weight of the animal. PanaKare Plus is added to moistened food (canned or dry). Thorough mixing is necessary to bring the enzymes into close contact with the food particles. After mixing, let stand at room temperature for 15-20 minutes.

Average dose/meal:

Dogs: 3/4-1 teaspoon (2.8g/teaspoon)

Cats: 1/4-3/4 teaspoon

STORAGE AND HANDLING

Store tightly closed container in a dry place at temperatures not exceeding 35°C (95°F).

PRINCIPAL DISPLAY PANEL - 4 oz Bottle

NDC: 59051-9064-1

PanaKare Plus Powder

Pancreatic Enzyme Concentrate

CAUTION: Federal law restricts this drug to use by or on the order of a licensed veterinarian.

Net Contents: 4 oz Powder (113 g)

PRINCIPAL DISPLAY PANEL - 8 oz Bottle

NDC: 59051-9064-2

PanaKare Plus Powder
Pancreatic Enzyme Concentrate

CAUTION: Federal law restricts this drug to use by or on the order of a licensed veterinarian.

Net Contents: 8 oz Powder (227 g)

PRINCIPAL DISPLAY PANEL - 12 oz Bottle

NDC: 59051-9064-3

PanaKare Plus Powder

Pancreatic Enzyme Concentrate

CAUTION: Federal law restricts this drug to use by or on the order of a licensed veterinarian.

Net Contents: 12 oz Powder (340.2 g)